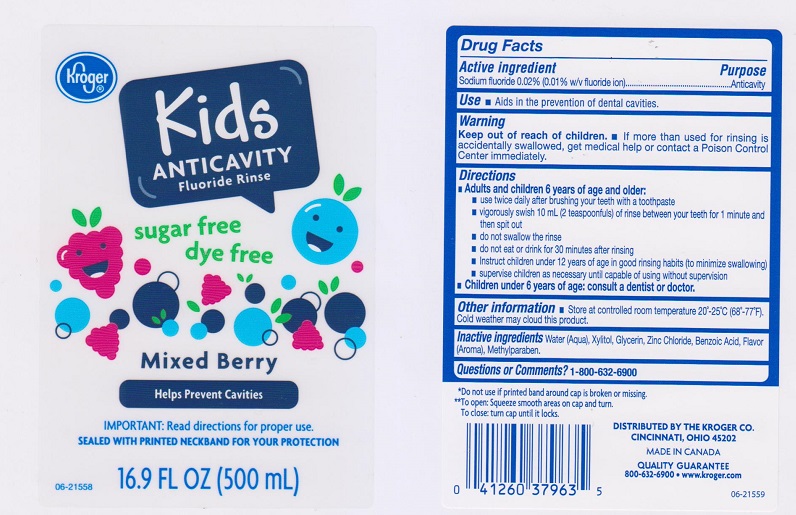 DRUG LABEL: Kroger Kids Anticavity Fluoride
NDC: 30142-563 | Form: LIQUID
Manufacturer: The Kroger Company
Category: otc | Type: HUMAN OTC DRUG LABEL
Date: 20170123

ACTIVE INGREDIENTS: SODIUM FLUORIDE 0.2 mg/1 mL
INACTIVE INGREDIENTS: WATER; XYLITOL; GLYCERIN; ZINC CHLORIDE; BENZOIC ACID; METHYLPARABEN

Drug Facts

Active ingredient

Sodium fluoride 0.02% (0.01% w/v fluoride ion)

Purpose

Anticavity

Use

- Aids in the prevention of dental cavities.

Warnings

Keep out of reach of children.

- If more than used for rinsing is accidentally swallowed, get medical help or contact a Poison Control Center immediately.

Directions

- Adults and children 6 years of age and older:
- use twice daily after brushing your teeth with a toothpaste
- vigorously swish 10 mL (2 teaspoonfuls) of rinse between your teeth for 1 minute and then spit out
- do not swallow the rinse
- do not eat or drink for 30 minutes after rinsing
- instruct children under 12 years of age in good rinsing habits (to minimize swallowing)
- supervise children as necessary until capable of using without supervision
- Children under 6 years of age: consult a dentist or doctor

Other information

- Store at controlled room temperature 20°-25°C (68°-77°F)
- Cold weather may cloud this product.

Inactive ingredients

Water (Aqua), Xylitol, Glycerin, Zinc Chloride, Benzoic Acid, Flavor (Aroma), Methylparaben.

Questions or Comments?

1-800-632-6900